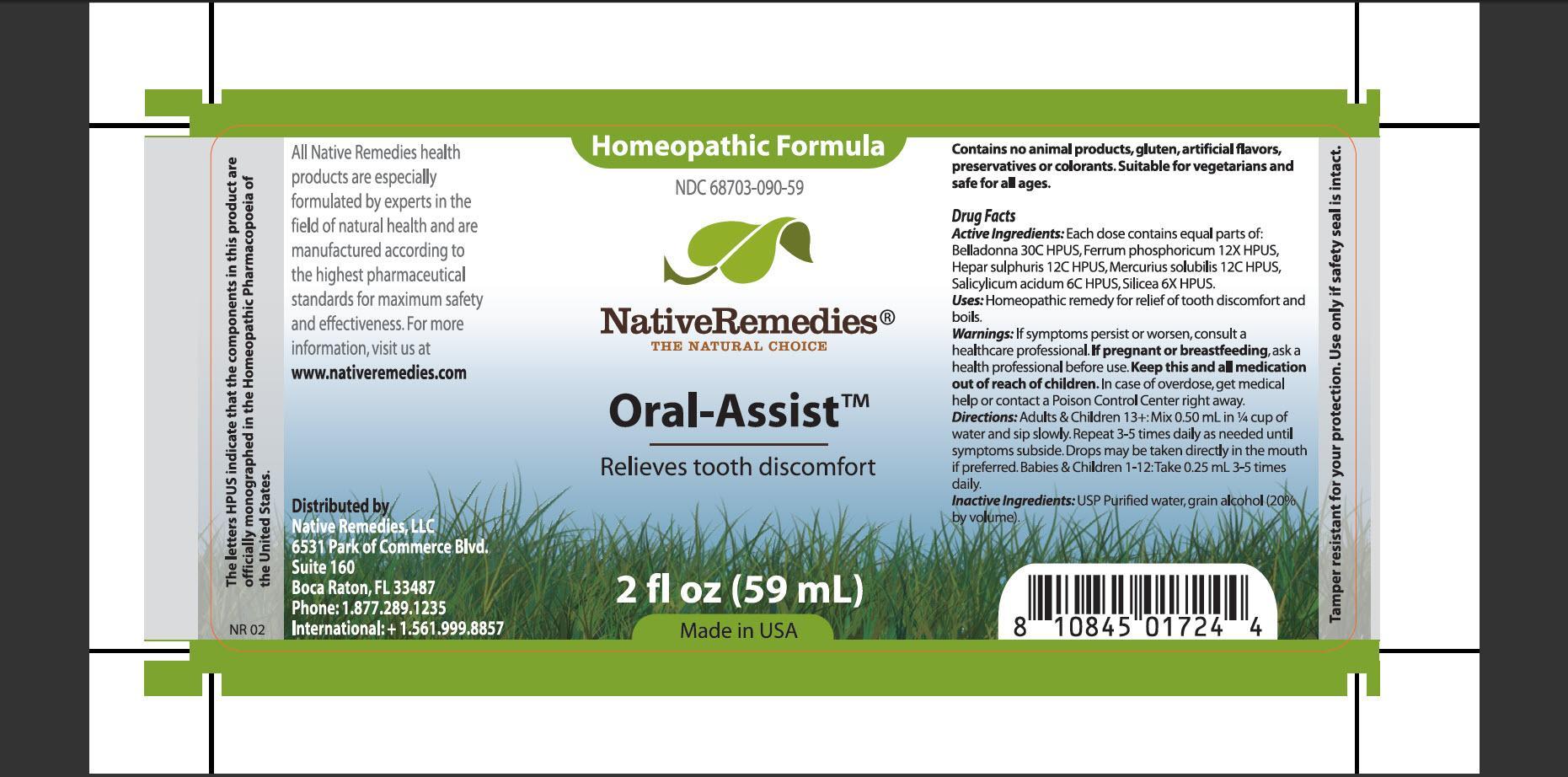 DRUG LABEL: Oral Assist
NDC: 68703-090 | Form: TINCTURE
Manufacturer: Native Remedies, LLC
Category: homeopathic | Type: HUMAN OTC DRUG LABEL
Date: 20130409

ACTIVE INGREDIENTS: ATROPA BELLADONNA 30 [hp_C]/1 mL; FERROSOFERRIC PHOSPHATE 12 [hp_X]/1 mL; CALCIUM SULFIDE 12 [hp_C]/1 mL; MERCURIUS SOLUBILIS 12 [hp_C]/1 mL; SALICYLIC ACID 6 [hp_C]/1 mL; SILICON DIOXIDE 6 [hp_X]/1 mL
INACTIVE INGREDIENTS: WATER; ALCOHOL

Oral Assist

PURPOSE

Relieves tooth disconfort

ACTIVE INGREDIENT

Active Ingredients: Each dose contains equal parts of: Belladonna 30C HPUS, Ferrum phosphoricum 12X HPUS, Hepar sulphuris 12C HPUS, Mercurius solubilis 12C HPUS, Salicylicum acidum 6C HPUS, Silicea 6X HPUS

INDICATIONS AND USAGE

Uses: Homeopathic remedy for relief of tooth discomfort and boils

WARNINGS

Warnings: If symptoms persist or worsen, consult a heathcare professional

PREGNANCY OR BREAST FEEDING

If pregnant or breastfeeding, ask a health professional before use

KEEP OUT OF REACH OF CHILDREN

Keep this and all medication out of reach of children

OVERDOSAGE

In case of overdose, get medical help or contact a Poison Control Center right away

DOSAGE AND ADMINISTRATION

Directions: Adults and Children 13+: Mix 0.50 mL in 1/4 cup of water and sip slowly. Repeat 3-5 times daily as needed until symptoms subside. Drops may be taken directly in the mouth if preferred. Babies and Children 1-12: Take 0.25 mL 3-5 times daily

INACTIVE INGREDIENT

Inactive Ingredients: USP Purified water, grain alcohol (20% by volume)

PATIENT COUNSELING INFORMATION

The letters HPUS indicated that the components in this product are officially monographed in the Homeopathic Pharmacopoeia of the United States

All Native Remedies health products are especially formulated by experts in the field of natural health and are manufactured according to the highest pharmaceutical standards for maximum safety and effectiveness. For more information, visit us at www.nativeremedies.com

Distributed by
Native Remedies, LLC
6531 Park of Commerce Blvd.
Suite 160
Boca Raton, FL 33487
Phone: 1.877.289.1235
International:+1.561.999.8857

Contains no animal products, gluten, artificial flavors, preservatives or colorants. Suitable for vegetarians and safe for all ages

STORAGE AND HANDLING

Tamper resistant for you protection. Use only if safety seal is intact